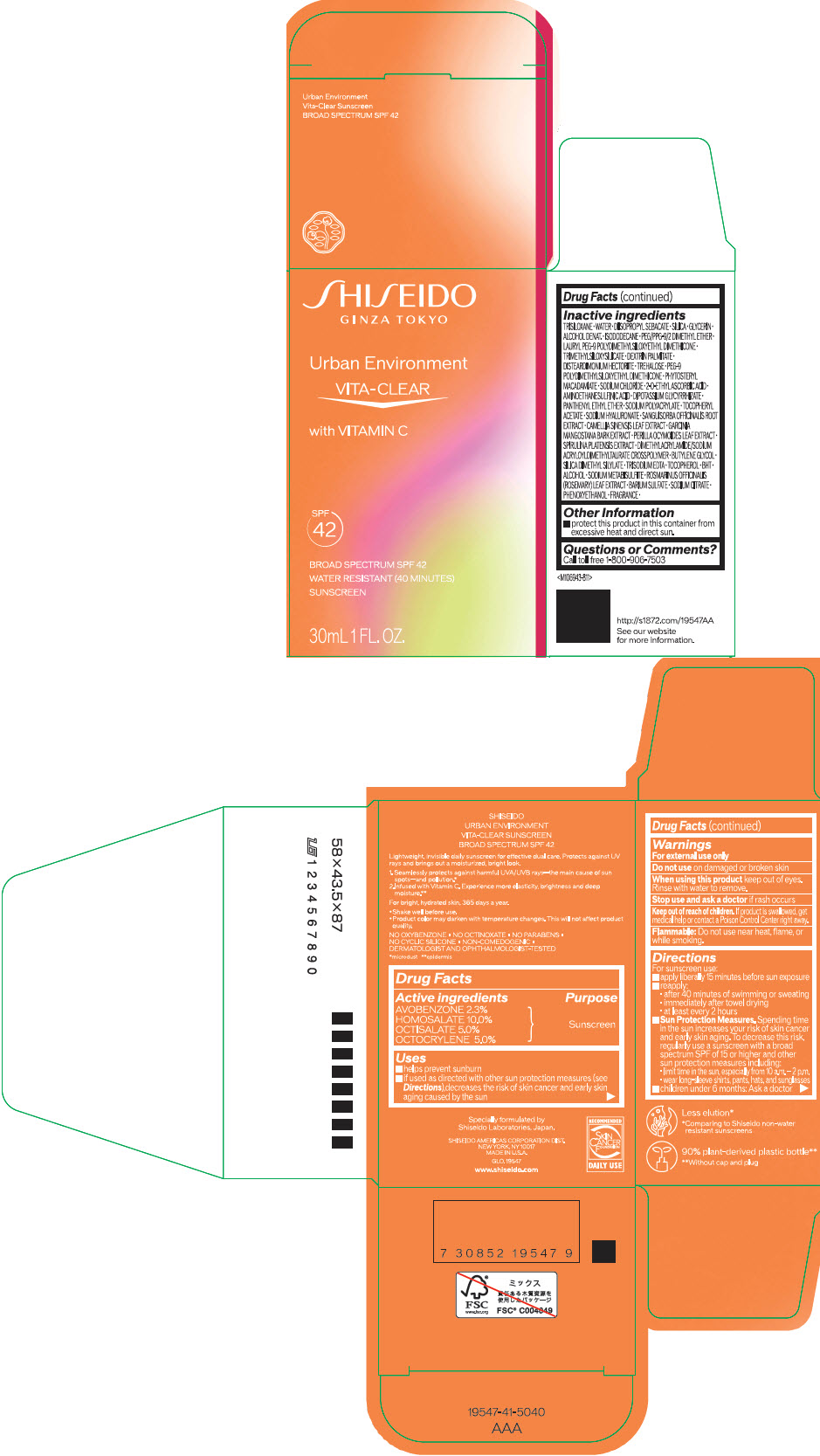 DRUG LABEL: SHISEIDO URBAN ENVIRONMENT VITA-CLEAR SUNSCREEN
NDC: 58411-854 | Form: EMULSION
Manufacturer: SHISEIDO AMERICAS CORPORATION
Category: otc | Type: HUMAN OTC DRUG LABEL
Date: 20260204

ACTIVE INGREDIENTS: AVOBENZONE 690 mg/30 mL; HOMOSALATE 3000 mg/30 mL; OCTISALATE 1500 mg/30 mL; OCTOCRYLENE 1500 mg/30 mL
INACTIVE INGREDIENTS: TRISILOXANE; WATER; DIISOPROPYL SEBACATE; SILICON DIOXIDE; GLYCERIN; ALCOHOL; ISODODECANE; PEG/PPG-9/2 DIMETHYL ETHER; LAURYL PEG-9 POLYDIMETHYLSILOXYETHYL DIMETHICONE; DISTEARDIMONIUM HECTORITE; TREHALOSE; PEG-9 POLYDIMETHYLSILOXYETHYL DIMETHICONE; PHYTOSTERYL MACADAMIATE; SODIUM CHLORIDE; 2-O-ETHYL ASCORBIC ACID; HYPOTAURINE; GLYCYRRHIZINATE DIPOTASSIUM; PANTHENYL ETHYL ETHER; .ALPHA.-TOCOPHEROL ACETATE; HYALURONATE SODIUM; SANGUISORBA OFFICINALIS ROOT; GREEN TEA LEAF; GARCINIA MANGOSTANA BARK; PERILLA FRUTESCENS LEAF; BUTYLENE GLYCOL; SILICA DIMETHYL SILYLATE; EDETATE TRISODIUM; TOCOPHEROL; BUTYLATED HYDROXYTOLUENE; SODIUM METABISULFITE; ROSEMARY; BARIUM SULFATE; SODIUM CITRATE, UNSPECIFIED FORM; PHENOXYETHANOL

SHISEIDO URBAN ENVIRONMENT VITA-CLEAR SUNSCREEN SPF 42

Drug Facts

ACTIVE INGREDIENT

Active ingredients | Purpose
AVOBENZONE 2.3% | Sunscreen
HOMOSALATE 10.0% | Sunscreen
OCTISALATE 5.0% | Sunscreen
OCTOCRYLENE 5.0% | Sunscreen

Uses

- helps prevent sunburn
- if used as directed with other sun protection measures (see Directions), decreases the risk of skin cancer and early skin aging caused by the sun

Warnings

For external use only

Do not useon damaged or broken skin

WHEN USING

When using this productkeep out of eyes. Rinse with water to remove.

Stop use and ask a doctorif rash occurs

Keep out of reach of children.If product is swallowed, get medical help or contact a Poison Control Center right away.

Flammable

Do not use near heat, flame, or while smoking.

Directions

For sunscreen use:

- apply liberally 15 minutes before sun exposure
- reapply:
  - after 40 minutes of swimming or sweating
  - immediately after towel drying
  - at least every 2 hours
- Sun Protection Measures. Spending time in the sun increases your risk of skin cancer and early skin aging. To decrease this risk, regularly use a sunscreen with a broad spectrum SPF value of 15 or higher and other sun protection measures including:
  - limit time in the sun, especially from 10 a.m. – 2 p.m.
  - wear long-sleeve shirts, pants, hats, and sunglasses
- children under 6 months: Ask a doctor

Inactive Ingredients

TRISILOXANE･WATER･DIISOPROPYL SEBACATE･SILICA･GLYCERIN･ALCOHOL DENAT.･ISODODECANE･PEG/PPG-9/2 DIMETHYL ETHER･LAURYL PEG-9 POLYDIMETHYLSILOXYETHYL DIMETHICONE･TRIMETHYLSILOXYSILICATE･DEXTRIN PALMITATE･DISTEARDIMONIUM HECTORITE･TREHALOSE･PEG-9 POLYDIMETHYSILOXYETHYL DIMETHICONE･PHYTOSTERYL MACADAMIATE･SODIUM CHLORIDE･2-O-ETHYLASCORBIC ACID･AMINOETHANESULFINIC ACID･DIPOTASSIUM GLYCYRRHIZATE･PANTHENYL ETHYL ETHER･SODIUM POLYACRYLATE･TOCOPHERYL ACETATE･SODIUM HYALURONATE･SANGUISORBA OFFICINALIS ROOT EXTRACT･CAMELLIA SINENSIS LEAF EXTRACT･GARCINIA MANGOSTANA BARK EXTRACT･PERILLA OCYMOIDES LEAF EXTRACT･SPIRULINA PLATENSIS EXTRACT･DIMETHYLACRYLAMIDE/SODIUM ACRYLOYLDIMETHYLTAURATE CROSSPOLYMER･BUTYLENE GLYCOL･SILICA DIMETHYL SILYLATE･TRISODIUM EDTA･TOCOPHEROL･BHT･ALCOHOL･SODIUM METABISULFITE･ROSMARINUS OFFICINALIS (ROSEMARY) LEAF EXTRACT･BARIUM SULFATE･SODIUM CITRATE･PHENOXYETHANOL･FRAGRANCE･

Other information

- protect this product in this container from excessive heat and direct sun.

Questions or Comments?

Call toll free 1-800-906-7503

PRINCIPAL DISPLAY PANEL - 30 mL Bottle Carton

SHISEIDO
GINZA TOKYO

Urban Environment

VITA-CLEAR

with VITAMIN C

SPF
42

BROAD SPECTRUM SPF 42
WATER RESISTANT (40 MINUTES)
SUNSCREEN

30mL 1 FL. OZ.